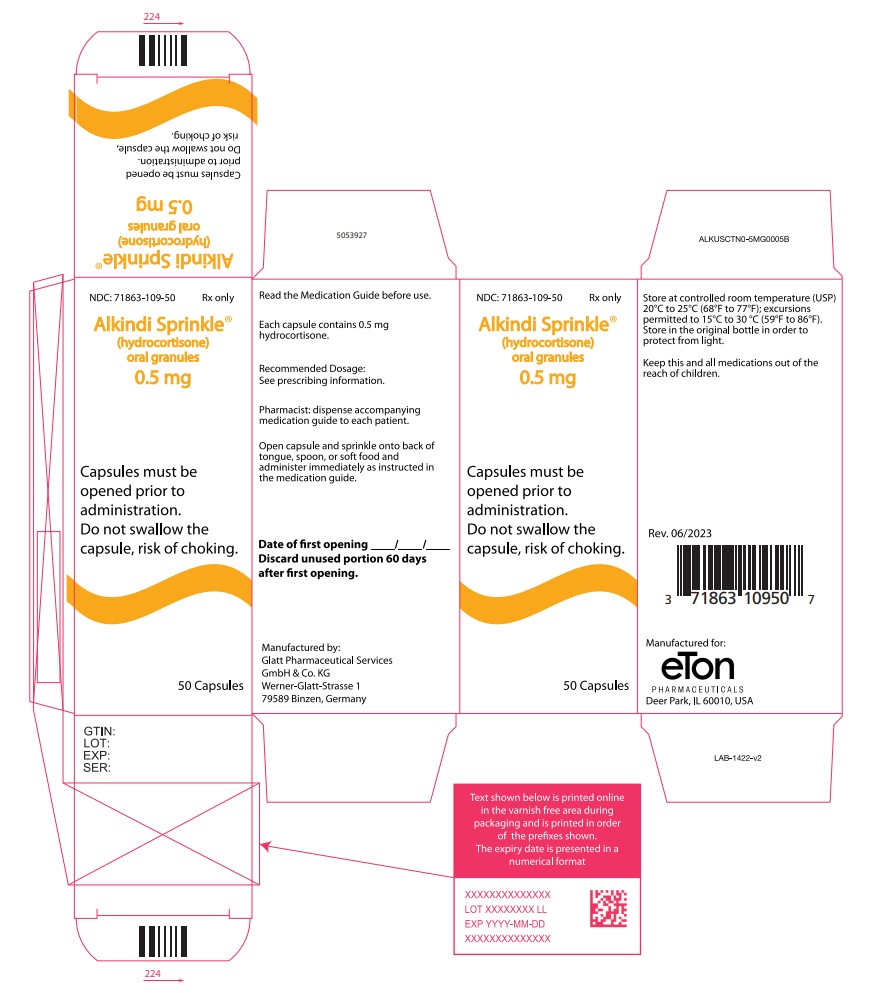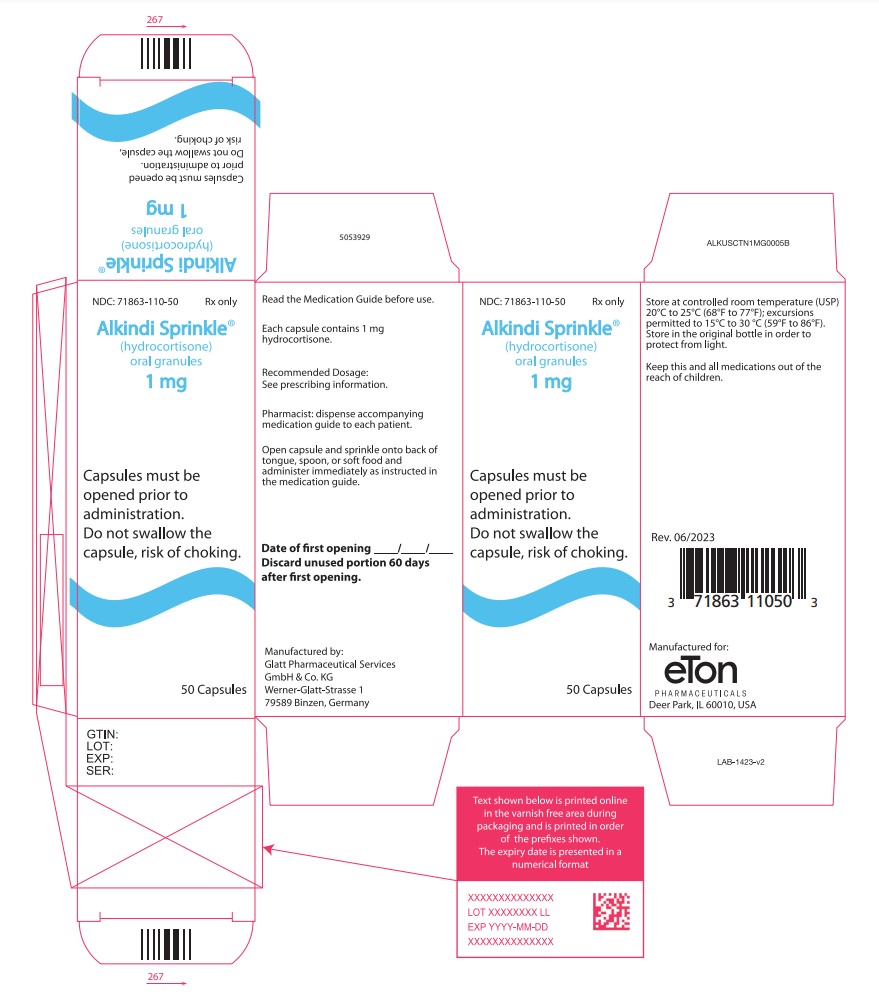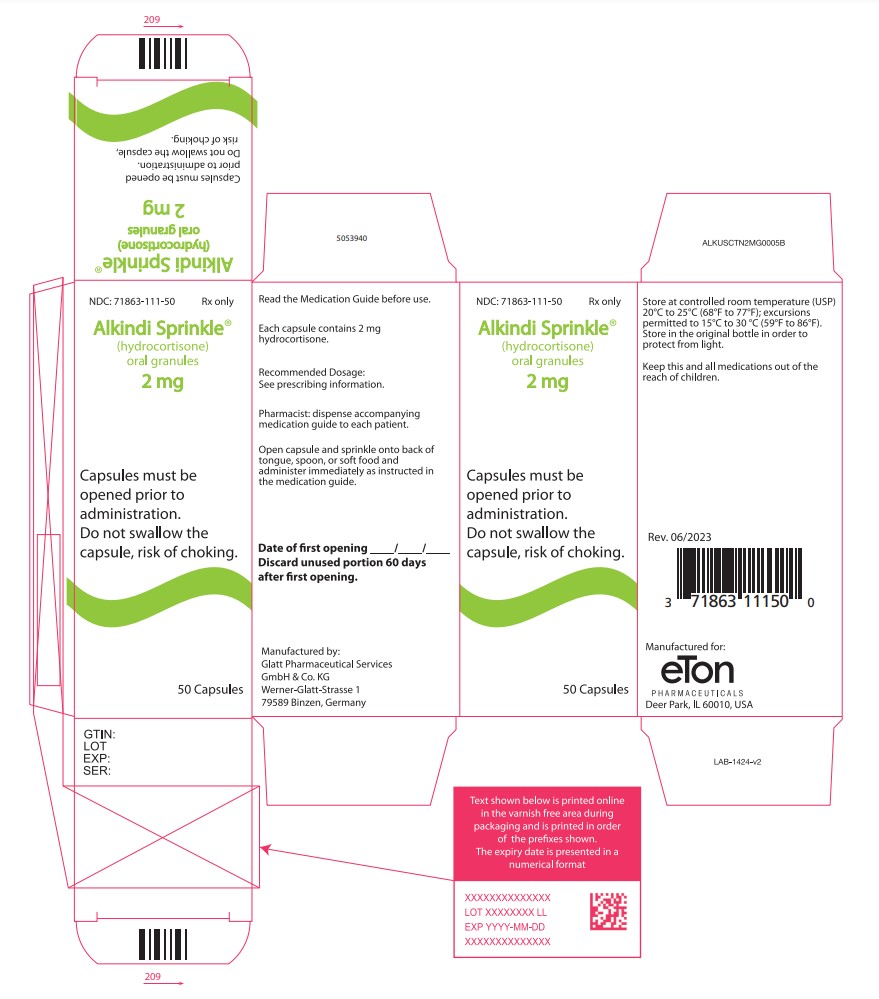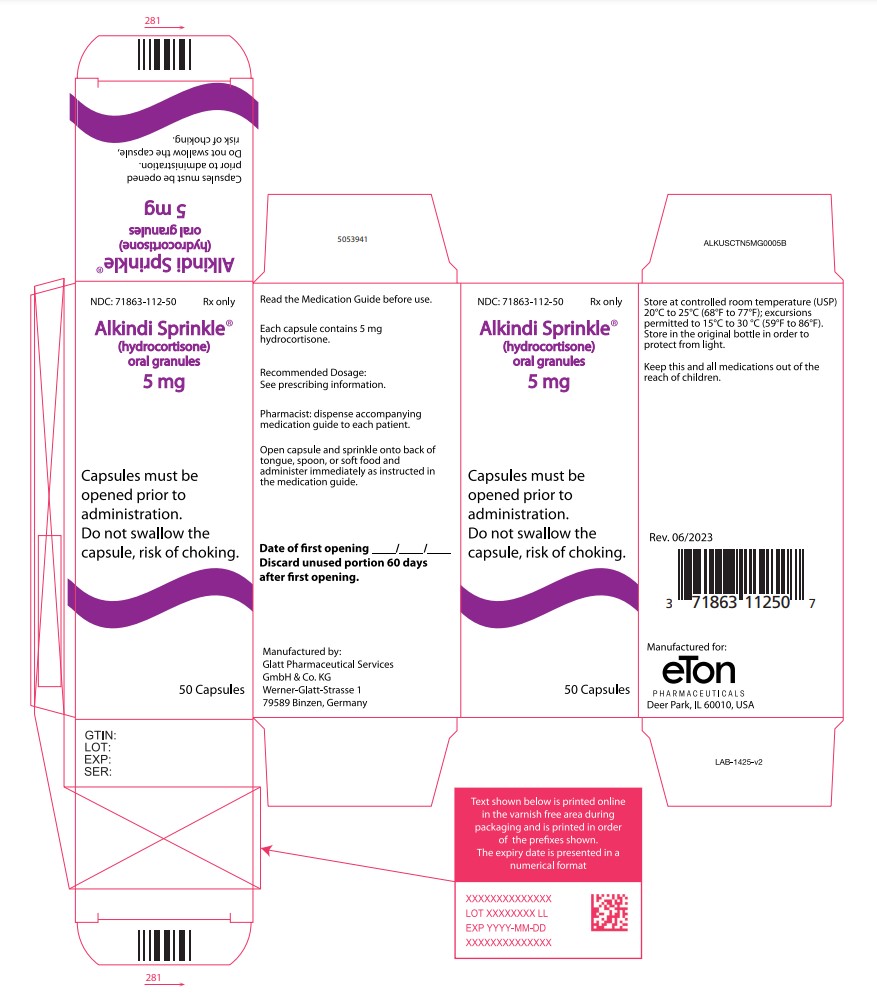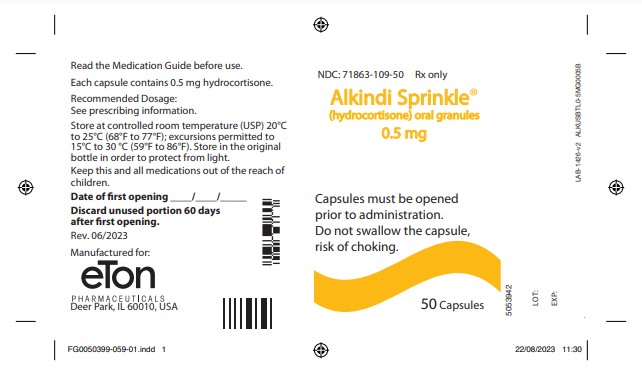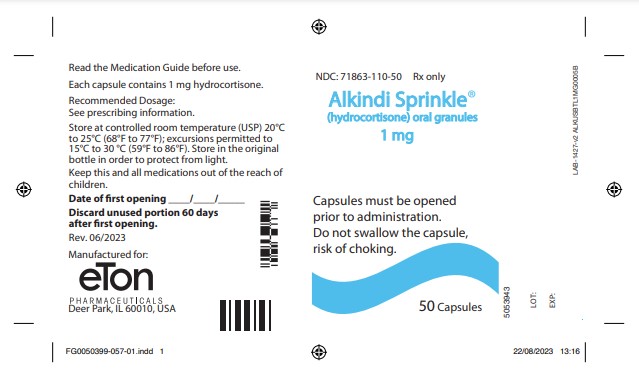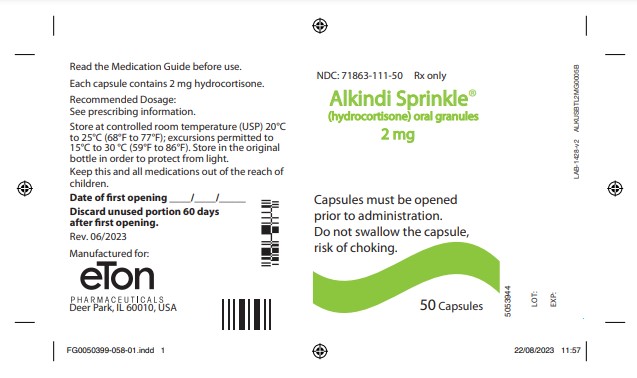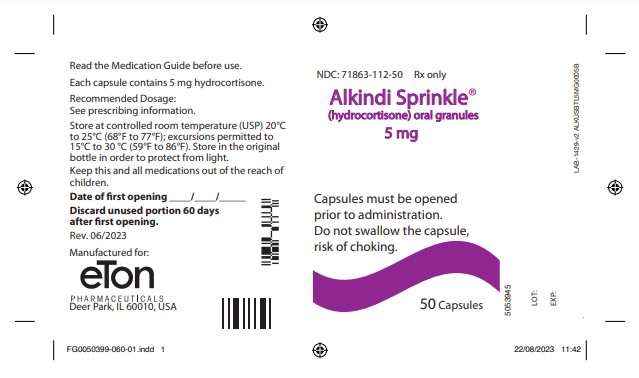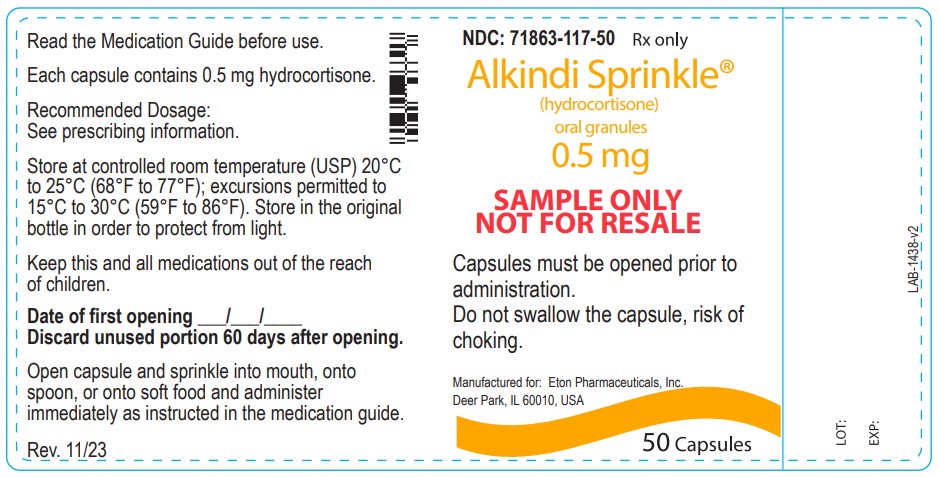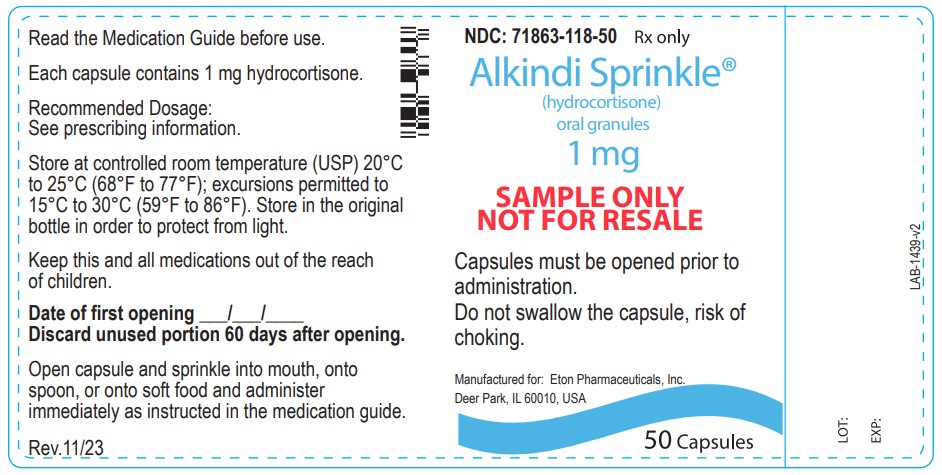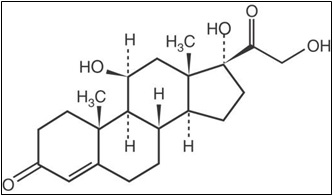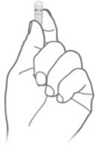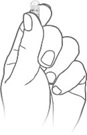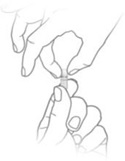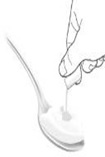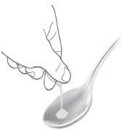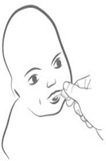 DRUG LABEL: Alkindi

NDC: 71863-109 | Form: GRANULE
Manufacturer: Eton Pharmaceuticals, Inc.
Category: prescription | Type: HUMAN PRESCRIPTION DRUG LABEL
Date: 20260107

ACTIVE INGREDIENTS: HYDROCORTISONE 0.5 mg/1 1
INACTIVE INGREDIENTS: MICROCRYSTALLINE CELLULOSE; HYPROMELLOSE, UNSPECIFIED; MAGNESIUM STEARATE; ETHYLCELLULOSE, UNSPECIFIED

HIGHLIGHTS OF PRESCRIBING INFORMATION

These highlights do not include all the information needed to use ALKINDI SPRINKLE ® safely and effectively. See full prescribing information for ALKINDI SPRINKLE ®.
ALKINDI SPRINKLE ® (hydrocortisone) oral granules
Initial U.S. Approval: 1952

Recent Major Changes

Warnings and Precautions (5.2, 5.9, 5.10) 02/2024

1 INDICATIONS AND USAGE

ALKINDI SPRINKLE is a corticosteroid indicated as replacement

therapy in pediatric patients with adrenocortical insufficiency. (1)

2 DOSAGE AND ADMINISTRATION

• Individualize the dose, using the lowest possible dosage. (2.1)
• The recommended starting replacement dosage is 8 to 10 mg/m2
daily. Higher doses may be needed based on patient’s age and
symptoms of the disease. Use of lower starting doses may be
sufficient in patients with residual but decreased endogenous
cortisol production. (2.1)
• Round the dose to the nearest 0.5 mg or 1 mg. More than one
capsule may be needed to supply the required dose. (2.1)
• Divide the total daily dose in 3 doses and administer 3 times daily.
Older patients may have their daily dose divided by 2 and
administered twice daily. (2.1)
• When switching from other oral hydrocortisone formulations, use
the same total daily hydrocortisone dosage. If symptoms of
adrenal insufficiency occur, increase total daily dosage. (2.2)
• ALKINDI SPRINKLE are oral granules contained within capsules.
Do not swallow the capsule. Do not chew or crush the granules.
(2.3)
• See the Full Prescribing Information for detailed administration
instructions. (2.3)

3 DOSAGE FORMS AND STRENGTHS

- Oral granules: 0.5 mg, 1 mg, 2 mg, 5 mg contained in capsules. (3)

4 CONTRAINDICATIONS

- Hypersensitivity to hydrocortisone or to any of the ingredients in

ALKINDI SPRINKLE. (4)

5 WARNINGS AND PRECAUTIONS

- Adrenal Crisis:Undertreatment, sudden discontinuation of therapy,

or switching from another oral hydrocortisone formulation may lead

to adrenocortical insufficiency, adrenal crisis and death. Adrenal

crisis may also be induced by stress events such as infections or

surgery. Increase the dose during periods of stress. Switch patients

who are vomiting, severely ill or unable to take oral medications to

parenteral corticosteroid formulations. (5.1)

- Immunosuppression and Increased Risk of Infection with Use of a

Dosage Greater Than Replacement: Use of a greater than

replacement dosage can suppress the immune system and increase

the risks of new infections or exacerbation of latent infections with

any pathogen, including viral, bacterial, fungal, protozoan, or helminthic

infections. Monitor patients for signs and symptoms of infections. (5.2)

- Growth Retardation:Long-term use in excessive doses may cause

growth retardation. Use the minimum dosage of ALKINDI

SPRINKLE to achieve desired clinical response and monitor the

patient’s growth. (5.3)

- Cushing’s Syndrome Due to Use of Excessive Doses of

Corticosteroids:Prolonged use with supraphysiologic doses may

cause Cushing’s syndrome. Monitor patients for signs and
symptoms of Cushing’s syndrome every 6 months, pediatric patients

under one year of age may require more frequent monitoring. (5.4)

- Decrease in Bone Mineral Density:Corticosteroids decrease bone

formation and increase bone resorption which may lead to inhibition

of bone growth and development of osteoporosis. Use the minimum

dosage of ALKINDI SPRINKLE to achieve desired clinical response. (5.5)

- Psychiatric Adverse Reactions:Use may be associated with severe

psychiatric adverse reactions such as euphoria, mania, psychosis

with hallucinations and delirium or depression. Symptoms typically

emerge within a few days or weeks of starting the treatment. Most

reactions resolve after either dose reduction or withdrawal, although

specific treatment may be necessary. Monitor patients for behavioral

and mood disturbances during treatment. Instruct caregivers and/or

patients to seek medical advice if psychiatric symptoms develop. (5.6)

- Ophthalmic Adverse Reactions:Cataracts, glaucoma and central

serous chorioretinopathy have been reported with prolonged use of

high doses. Monitor patients for blurred vision or other visual

disturbances and if they occur, refer them to an ophthalmologist. (5.7)

- Gastrointestinal Adverse Reactions:Increased risk in patients with

certain gastrointestinal disorders. Signs and symptoms may be

masked. (5.8)

6 ADVERSE REACTIONS

Common adverse reactions for corticosteroids include fluid retention,

alteration in glucose tolerance, elevation in blood pressure, behavioral

and mood changes, increased appetite and weight gain. (6)

To report SUSPECTED ADVERSE REACTIONS, contact Eton

Pharmaceuticals, Inc. at 1-855-224-0233 or FDA at 1-800-FDA-1088

or www.fda.gov/medwatch.

7 DRUG INTERACTIONS

- CYP3A4 Inhibitors: concomitant administration may require a

decrease in the ALKINDI SPRINKLE dose. (7)

- CYP3A4 Inducers: concomitant administration may require an

increase in the ALKINDI SPRINKLE dose. (7)

- Estrogen and Estrogen Containing Products: concomitant

administration may require an increase in the ALKINDI SPRINKLE dose. (7)

- Antidiabetic agents:excessive doses may increase blood glucose

concentrations. Dose adjustment of antidiabetic agents may be

required. (7)

- NSAIDs:concomitant administration increases risk of

gastrointestinal adverse reactions. (7)

See 17 for PATIENT COUNSELING INFORMATION and

FDA-approved patient labeling (Medication Guide).

Revised 12/2024

FULL PRESCRIBING INFORMATION

1 INDICATIONS AND USAGE

ALKINDI SPRINKLE is indicated as replacement therapy in pediatric patients with adrenocortical insufficiency.

2 DOSAGE AND ADMINISTRATION

'

2.1 Dosage Information

- Individualize the dose for each patient, using the lowest possible dosage.
- The recommended starting replacement dosage is 8 to 10 mg/m^2/day daily. Higher doses may be needed based on patient’s age and symptoms of the disease. Use of lower starting doses may be sufficient in patients with residual but decreased endogenous cortisol production.
- Round the dose to the nearest 0.5 mg or 1 mg. The contents of more than one capsule may be needed to supply the required dose.
- Divide the total daily dose in 3 doses and administer 3 times daily. Older pediatric patients may have their daily dose divided by 2 and administered twice daily.
- Monitor patients for symptoms of under and/or overtreatment including signs and symptoms of adrenocortical insufficiency, linear growth and weight gain. Adjust doses accordingly.
- During episodes of acute febrile illness, gastroenteritis, surgery or major trauma, patients may need increased doses [see Warnings and Precautions (5.1)] .

2.2 Switching to ALKINDI SPRINKLE from Other Oral Hydrocortisone Formulations

When switching patients from other oral hydrocortisone formulations to ALKINDI SPRINKLE, use the same total daily hydrocortisone dosage. Closely monitor patients after switching to ALKINDI SPRINKLE for symptoms of adrenocortical insufficiency. If
symptoms of adrenal insufficiency occur after switching, increase the total daily dosage of ALKINDI SPRINKLE [see Warnings and Precautions (5.1)].

2.3 Administration Instructions

- ALKINDI SPRINKLE are oral granules contained within capsules.
- Do not swallow the capsules. Do not chew or crush the granules.
- Do not use ALKINDI SPRINKLE granules in nasogastric or gastric tubes as they may

cause tube blockage.

- Open the capsule and administer the granules as follows:
  - Hold the capsule so that the printed strength is at the top and tap to ensure all

the granules are in the lower half of the capsule.

- Squeeze the bottom of the capsule gently and twist off the top of the capsule.
- The granules may be administered by pouring the granules directly onto the

patient’s tongue, pouring the granules onto a spoon and placing in the patient’s
mouth, or sprinkling onto a spoonful of cold or room temperature soft food (such as
yogurt or fruit puree). The granules should be given and swallowed within 5 minutes
to avoid a bitter taste as the outer taste masking cover can dissolve.

- Tap the capsule to ensure all the granules are removed. Avoid wetting the capsule

on the tongue or soft food as this may result in granules remaining in the capsule.

- Immediately follow administration with ingestion of fluids such as water, milk, breast

milk or formula to ensure all granules are swallowed.

- Do not add the granules to liquid as this can result in reductions in the dose administered and

may result in a bitter taste.

- Instruct patients and/or caregivers to contact their healthcare provider if the full dose is not

administered (e.g., regurgitating, vomiting of granules). A repeat dose may be required to
avoid adrenal insufficiency [see Warnings and Precautions (5.1)].

3 DOSAGE FORMS AND STRENGTHS

ALKINDI SPRINKLE oral granules are white to off-white granules contained within transparent capsules and are available as follows:

Strength | Imprint on Capsules
0.5 mg | “INF-0.5” in red ink
1 mg | “INF-1.0” in blue ink
2 mg | “INF-2.0” in green ink
5 mg | “INF-5.0” in gray ink

4 CONTRAINDICATIONS

ALKINDI SPRINKLE is contraindicated in patients with hypersensitivity to hydrocortisone or to any of the ingredients in ALKINDI SPRINKLE. Anaphylactic reactions have occurred in patients receiving corticosteroids [see Adverse Reactions (6.2)] .

5 WARNINGS AND PRECAUTIONS

5.1 Adrenal Crisis

Undertreatment with ALKINDI SPRINKLE or sudden discontinuation of therapy with ALKINDI SPRINKLE may lead to adrenocortical insufficiency, adrenal crisis, and death. Adrenal crisis may also be induced by stress events such as infections or surgery when patients require higher doses of corticosteroids. Symptoms of adrenocortical insufficiency include poor feeding, fatigue, low muscle tone, joint pain, nausea, vomiting, hypoglycemia, low blood pressure and electrolyte disturbances.

Increase the dosage of ALKINDI SPRINKLE during periods of stress (infections, surgery). Switch patients who are vomiting, severely ill or unable to take oral medications to parenteral corticosteroid formulations without delay. Once the patient recovers, gradually reduce the steroid dosage used during the acute event.

When switching patients to ALKINDI SPRINKLE from another oral hydrocortisone formulation, consider the potential for dosing inaccuracy if the other oral hydrocortisone formulation has been manipulated (e.g., split or crushed tablets, compounded formulations). Manipulation of oral hydrocortisone formulations may result in a relative difference in hydrocortisone exposure when using the same dosage to initiate ALKINDI SPRINKLE treatment. Closely monitor patients after switching to ALKINDI SPRINKLE to ensure ALKINDI SPRINKLE is providing the same level of hydrocortisone exposure as the previously used oral hydrocortisone formulation. If symptoms of adrenal insufficiency occur, increase the total daily dosage of ALKINDI SPRINKLE.

5.2 Immunosuppression and Increased Risk of Infection with Use of a Dosage Greater Than Replacement

Use of the recommended dosage of ALKINDI SPRINKLE [see Dosage and Administration (2.1, 2.2)] as a replacement therapy in pediatric patients with adrenocortical insufficiency is not expected to cause immunosuppression or increase the risk of infection. The use of a greater than replacement dosage can suppress the immune system and increase the risk of infection with any pathogen, including viral, bacterial, fungal, protozoan, or helminthic pathogens. The use of ALKINDI SPRINKLE at greater than replacement dosage can:

• Reduce resistance to new infections

• Exacerbate existing infections

• Increase the risk of disseminated infections

• Increase the risk of reactivation or exacerbation of latent infections

• Mask some signs of infection

Infections associated with the use of corticosteroids at a greater than replacement dosage range

from mild to severe or fatal, and the rate of infectious complications increases with increasing

corticosteroid dosages.

Monitor for the development of infection and consider ALKINDI SPRINKLE dosage reduction as

needed.

5.3 Growth Retardation

Long-term use of corticosteroids in excessive doses may cause growth retardation in pediatric patients. Historical cohorts of adults treated from childhood for congenital adrenal hyperplasia have been found to have growth retardation. Effects on linear growth are less likely when using corticosteroids as replacement therapy. Use the minimum dosage of ALKINDI SPRINKLE to achieve desired clinical response and monitor the patient’s growth.

5.4 Cushing’s Syndrome Due to Use of Excessive Doses of Corticosteroids

Prolonged use of corticosteroids in supraphysiologic doses may cause Cushing’s syndrome. Symptoms and signs of Cushing’s syndrome include weight gain, decreased height velocity, hyperglycemia, hypertension, edema, easy bruising, muscle weakness, red round face, depression or mood swings. Monitor patients for signs and symptoms of Cushing’s syndrome every 6 months; pediatric patients under one year of age may require more frequent monitoring, e.g., every 3 to 4 months.

5.5 Decrease in Bone Mineral Density

Corticosteroids decrease bone formation and increase bone resorption which may lead to development of osteoporosis. Historical cohorts of adults treated from childhood for congenital adrenal hyperplasia have been found to have reduced bone mineral density and increased fracture rates. Use the minimum dosage of ALKINDI SPRINKLE to achieve desired clinical response.

5.6 Psychiatric Adverse Reactions

Corticosteroid use may be associated with severe psychiatric adverse reactions. Euphoria, mania, psychosis with hallucinations and delirium or depression have been seen in patients at replacement doses of hydrocortisone [see Adverse Reactions (6)] . Symptoms typically emerge within a few days or weeks of starting the treatment. Risks may be higher with high doses, although dose levels do not allow prediction of the onset, type, severity or duration of reactions. Most reactions resolve after either dose reduction or withdrawal, although specific treatment may be necessary. Monitor patients for behavioral and mood disturbances during treatment with ALKINDI SPRINKLE. Instruct caregivers and/or patients to seek medical advice if psychiatric symptoms develop.

5.7 Ophthalmic Adverse Reactions

Ophthalmic effects, such as cataract, glaucoma or central serous chorioretinopathy have been reported with prolonged use of corticosteroids in high doses. Monitor patients for blurred vision or other visual disturbances. If patients develop ophthalmic adverse reactions, refer them to an ophthalmologist for further evaluation.

5.8 Gastrointestinal Adverse Reactions

There is an increased risk of gastrointestinal perforation in patients with certain gastrointestinal disorders. Signs of gastrointestinal perforation, such as peritoneal irritation may be masked in patients receiving corticosteroids. Corticosteroids should be used with caution if there is a probability of impending perforation, abscess, or other pyogenic infections; diverticulitis; fresh intestinal anastomoses; and active or latent peptic ulcer.

Concurrent administration of corticosteroids with non-steroidal anti-inflammatory drugs (NSAIDS) may increase the risk of gastrointestinal adverse reactions. Monitor patients receiving corticosteroids and concomitant NSAIDS for gastrointestinal adverse reactions [see Drug Interactions (7)] .

5.9 Risk of Kaposi’s Sarcoma with Use of a Dosage Greater Than Replacement

Kaposi’s sarcoma has been reported to occur in patients receiving corticosteroid therapy, most often

for chronic conditions at a dosage greater than replacement (supraphysiologic dosage). If patients

take a supraphysiologic chronic dosage of ALKINDI SPRINKLE, they are at increased risk of

developing Kaposi’s sarcoma.

5.10 Vaccination

Administration of live vaccines may be acceptable in ALKINDI SPRINKLE-treated pediatric patients

with adrenocortical insufficiency who receive replacement corticosteroids.

6 ADVERSE REACTIONS

The following serious adverse reactions are described here and elsewhere in the label:

- Adrenal Crisis [see Warnings and Precautions (5.1)]
- Immunosuppression and Increased Risk of Infection with Use of a Dosage Greater Than Replacement [see Warnings and Precautions (5.2)]
- Growth Retardation [see Warnings and Precautions (5.3)]
- Cushing’s Syndrome Due to Use of Excessive Doses of Corticosteroids [see Warnings and Precautions (5.4)]
- Decrease in Bone Mineral Density [see Warnings and Precautions (5.5)]
- Psychiatric Adverse Reactions [see Warnings and Precautions (5.6)]
- Ophthalmic Adverse Reactions [see Warnings and Precautions (5.7)]
- Gastrointestinal Adverse Reactions [see Warnings and Precautions (5.8)]
- Risk of Kaposi's Sarcoma with Use of Dosage Greater Than Replacement [see Warnings and Precautions (5.9)]
- Vaccinations [see Warnings and Precautions (5.10)]

6.1 Clinical Trials Experience

Because clinical studies are conducted under widely varying conditions, adverse reaction rates observed in the clinical trials of a drug cannot be directly compared to rates in the clinical trials of another drug and may not reflect the rates observed in practice.

ALKINDI SPRINKLE was evaluated in an uncontrolled, open-label, single-arm clinical study in 18 pediatric patients with adrenocortical insufficiency. Adrenocortical insufficiency was due to congenital adrenal hyperplasia in 17 patients and to hypopituitarism in one patient. All patients received at least one dose of ALKINDI SPRINKLE. The age ranged from 36 days to 5.7 years at start of treatment; 8 patients were female and 10 were male; 100% were White. Adverse reactions that were reported in two or more patients (≥ 11%) are shown in Table 1.

Table 1 Adverse Reactions Occurring in >11% of Pediatric Patients with Adrenocortical Insufficiency Treated with ALKINDI SPRINKLE for up to 29 Months
Adverse Reactions | N=18 (%)
Pyrexia | 10 (56)
Gastroenteritis | 9 (50)
Viral upper respiratory tract infection | 8 (44)
Vomiting | 7 (39)
Viral infection | 6 (33)
Conjunctivitis | 5 (28)
Otitis media viral | 3 (17)
Tonsillitis | 3 (17)
Body temperature increased | 2 (11)
Bronchitis | 2 (11)
Dental caries | 2 (11)
Diarrhea | 2 (11)
Genitourinary operation | 2 (11)
Pharyngitis | 2 (11)
Respiratory tract infection | 2 (11)
Rhinitis | 2 (11)

6.2 Postmarketing Experience

The following adverse reactions seen in pediatric and adult patients associated with the use of corticosteroids were identified in the literature and from postmarketing reports. Because some of these reactions are reported voluntarily from a population of uncertain size, it is not always possible to reliably estimate their frequency or establish a causal relationship to drug exposure.

Common adverse reactions for corticosteroids include fluid retention, alteration in glucose tolerance, elevation in blood pressure, behavioral and mood changes, increased appetite and weight gain.

Allergic Reactions:Anaphylaxis, angioedema

Cardiovascular:Bradycardia, cardiac arrest, cardiac arrhythmias, cardiac enlargement, circulatory collapse, congestive heart failure, fat embolism, hypertension, hypertrophic cardiomyopathy in premature infants, myocardial rupture following recent myocardial infarction, pulmonary edema, syncope, tachycardia, thromboembolism, thrombophlebitis, vasculitis

Dermatologic:Acne, allergic dermatitis, cutaneous and subcutaneous atrophy, dry scalp, edema, facial erythema, hyper or hypo-pigmentation, impaired wound healing, increased sweating, petechiae and ecchymoses, rash, sterile abscess, striae, suppressed reactions to skin tests, thin fragile skin, thinning scalp hair, urticaria

Endocrine:Abnormal fat deposits, decreased carbohydrate tolerance, development of Cushingoid state, hirsutism, manifestations of latent diabetes mellitus and increased requirements for insulin or oral hypoglycemic agents in diabetics, menstrual irregularities, moon faces, secondary adrenocortical and pituitary unresponsiveness (particularly in times of stress, as in trauma, surgery or illness), suppression of growth in pediatric patients

Fluid and Electrolyte Disturbances:Fluid retention, potassium loss, hypertension, hypokalemic alkalosis, sodium retention

Gastrointestinal:Abdominal distention, elevation in serum liver enzymes levels (usually reversible upon discontinuation), hepatomegaly, hiccups, malaise, nausea, pancreatitis, peptic ulcer with possible perforation and hemorrhage, ulcerative esophagitis

General:Increased appetite and weight gain

Metabolic:Negative nitrogen balance due to protein catabolism

Musculoskeletal:Osteonecrosis of femoral and humeral heads, Charcot-like arthropathy, loss of muscle mass, muscle weakness, osteoporosis, pathologic fracture of long bones, steroid myopathy, tendon rupture, vertebral compression fractures

Neurological:Arachnoiditis, convulsions, depression, emotional instability, euphoria, headache, increased intracranial pressure with papilledema (pseudo-tumor cerebri) usually following discontinuation of treatment, insomnia, meningitis, mood swings, neuritis, neuropathy, paraparesis/paraplegia, paresthesia, personality changes, sensory disturbances, vertigo

Ophthalmic:Exophthalmos, glaucoma, increased intraocular pressure, posterior subcapsular cataracts, and central serous chorioretinopathy

Reproductive:Alteration in motility and number of spermatozoa

7 DRUG INTERACTIONS

Table 2 Drug Interactions with ALKINDI SPRINKLE
CYP3A4 Inhibitors
Clinical Impact: | Hydrocortisone is metabolized by cytochrome P450 3A4 (CYP3A4). Concomitant administration of inhibitors of CYP3A4 may lead to increases in serum concentrations of ALKINDI SPRINKLE and increase the risk of adverse reactions associated with the use of excessive doses.
Intervention: | Concomitant use of CYP3A4 inhibitors may require a decrease in the ALKINDI SPRINKLE dose.
Examples: | Anti-fungals:itraconazole, posaconazole, voriconazole Antibiotics:erythromycin and clarithromycin Antiretrovirals:ritonavir Grapefruit juice
CYP3A4 Inducers
Clinical Impact: | Hydrocortisone is metabolized by cytochrome P450 3A4 (CYP3A4). Concomitant administration of inducers of CYP3A4 may lead to decreases in serum concentrations of ALKINDI SPRINKLE and increase the risk of adverse reactions, including adrenal crisis.
Intervention: | Concomitant use of CYP3A4 inducers may require an increase in the ALKINDI SPRINKLE dose.
Examples: | Anticonvulsants:phenytoin, carbamazepine and oxcarbazepine Antibiotics:rifampicin and rifabutin Barbiturates:phenobarbital and primidone Antiretrovirals:efavirenz and nevirapine
Estrogen and Estrogen Containing Products
Clinical Impact: | Oral estrogen and estrogen-containing oral contraceptives may interact with hydrocortisone by increasing serum cortisol-binding globulin (CBG) concentration. Concomitant use may reduce the efficacy of ALKINDI SPRINKLE by binding and delaying or preventing absorption.
Intervention: | Concomitant use of estrogen/estrogen containing products may require an increase in the ALKINDI SPRINKLE dose.
Antidiabetic Agents
Clinical Impact: | Corticosteroids in supraphysiologic doses may increase blood glucose concentrations.
Intervention: | Use of ALKINDI SPRINKLE in supraphysiologic doses may require a dose adjustment of antidiabetic agents.
Anticoagulant Agents
Clinical Impact: | Concomitant use of warfarin and corticosteroids usually results in inhibition of response to warfarin, although there have been some conflicting reports.
Intervention: | Monitor coagulation indices in patients receiving ALKINDI SPRINKLE and concomitant warfarin to maintain the desired anticoagulant effect.
Cyclosporine
Clinical Impact: | Increased activity of both cyclosporine and corticosteroids may occur when the two are used concurrently. Convulsions have been reported with concurrent use.
Intervention: | Monitor patients receiving ALKINDI SPRINKLE and concomitant cyclosporine.
Nonsteroidal Anti-inflammatory Drugs (NSAIDs)
Clinical Impact: | Concomitant use of NSAIDs and corticosteroids increases the risk of gastrointestinal adverse reactions. Aspirin should be used cautiously in conjunction with corticosteroids in hypoprothrombinemia. The clearance of salicylates may be increased with concurrent use of corticosteroids; this could lead to decreased salicylate serum levels or increase the risk of salicylate toxicity when corticosteroid is withdrawn.
Intervention: | Monitor patients receiving ALKINDI SPRINKLE and concomitant NSAIDs.

8 USE IN SPECIFIC POPULATIONS

8.1 Pregnancy

Risk Summary

Untreated adrenocortical insufficiency in pregnancy can result in a high rate of complications, including maternal mortality. The use of physiologic doses of hydrocortisone is not expected to cause major birth defects, miscarriage and adverse maternal and fetal outcomes. Available data from observational studies with hydrocortisone use in pregnancy have not identified a clear drug-associated risk of major birth defects, miscarriage or adverse maternal or fetal outcomes (see Data).

The estimated background risk of major birth defects and miscarriage for the indicated population is unknown. In the U.S. general population, the estimated background risk of major birth defects and miscarriage in clinically recognized pregnancies is 2–4% and 15–20%, respectively.

Data

Human Data

Available data from observational studies with hydrocortisone use in pregnant women have not identified a clear drug-associated risk of major birth defects, miscarriage or adverse maternal or fetal outcomes. Evidence from published epidemiologic studies suggest that there may be a small increased risk of cleft lip with or without cleft palate associated with first trimester systemic corticosteroid use in pregnant patients. However, the data are limited and report inconsistent findings, and studies have important methodological limitations, including non-randomized design, retrospective data collection, lack of dose-response data and the inability to control for confounders,such as underlying maternal disease and use of concomitant medications. In addition, unlike other corticosteroids, hydrocortisone is enzymatically deactivated by the placenta and therefore, limits fetal exposure.

Animal Data

Corticosteroids have been shown to be teratogenic in many species when given in doses equivalent to the human dose. Animal studies in which corticosteroids have been given to pregnant mice, rats and rabbits without adrenocortical insufficiency have yielded an increased incidence of cleft palate in the offspring.

8.2 Lactation

Risk Summary

Cortisol is present in human milk. The use of hydrocortisone at a physiologic dose for adrenocortical insufficiency is not expected to adversely affect the breastfed infant or milk production. There are no data on the presence of hydrocortisone in breast milk, the effect on the breastfed infant or on milk production. The developmental and health benefits of breastfeeding should be considered along with the mother’s clinical need for ALKINDI SPRINKLE and any potential adverse effects on the breastfed infant from ALKINDI SPRINKLE or from the underlying maternal condition.

8.4 Pediatric Use

The safety and effectiveness of ALKINDI SPRINKLE have been established in pediatric patients for replacement therapy of adrenocortical insufficiency and the information on this use is discussed throughout the labeling. Use of ALKINDI SPRINKLE in pediatric patients is supported by use in pediatric patients for adrenocortical insufficiency with another hydrocortisone product, along with supportive pharmacokinetic and safety data in 24 pediatric patients with adrenocortical insufficiency. No new adverse reactions were identified [see Adverse Reactions (6) and Clinical Pharmacology (12.3)]. ALKINDI SPRINKLE are oral granules contained within capsules that must be opened and not swallowed whole to administer the granules. Additionally, ALKINDI SPRINKLE granules should not be administered via nasogastric or gastric tubes as they may cause tube blockage [see Dosage and Administration (2.2)].

10 OVERDOSAGE

Treatment of acute overdosage is by supportive and symptomatic therapy.

11 DESCRIPTION

ALKINDI SPRINKLE contains hydrocortisone, a corticosteroid, also known as cortisol. The chemical name of hydrocortisone is 11β,17α,21-trihydroxy-pregn-4-ene-3,20-dione and it has the chemical formula of C21H30O5, and molecular weight of 362 g·mol^−1. Hydrocortisone is a white or almost white powder soluble in the pH range of 1-7.

Structural formula of hydrocortisone:

ALKINDI SPRINKLE are oral granules contained within hard capsules. The inactive ingredients in the granules are microcrystalline cellulose, hypromellose, magnesium stearate and ethyl cellulose and the capsule shell contains hypromellose. The printing ink contains shellac, propylene glycol and concentrated ammonia solution. The printing ink also contains red iron oxide, potassium hydroxide for 0.5 mg (red), indigotine for 1 mg (blue), indigotine, yellow iron oxide, titanium dioxide for 2 mg (green) and titanium dioxide, black iron oxide, potassium hydroxide for 5 mg (gray).

12 CLINICAL PHARMACOLOGY

12.1 Mechanism of Action

Hydrocortisone is a glucocorticoid. Glucocorticoids, adrenocortical steroids, cause varied metabolic effects. In addition, they modify the body's immune responses to diverse stimuli..

12.2 Pharmacodynamics

Naturally occurring glucocorticoids (hydrocortisone and cortisone), which also have salt-retaining properties, are used as replacement therapy in adrenocortical deficiency states.

12.3 Pharmacokinetics

Absorption
Following oral administration, a dose of ALKINDI SPRINKLE 4x5 mg was approximately 87% bioavailable when compared to intravenous hydrocortisone in dexamethasone-suppressed healthy adult male volunteers. The median time to peak serum concentration (Tmax) was 0.75 hours post-dose following oral administration.

In an open label, single dose study in 24 pediatric patients with adrenocortical insufficiency, ALKINDI SPRINKLE (1-4 mg based on body surface area) increased cortisol levels from baseline to median cortisol level 19.4 mcg/dL (range 12.5 – 52.4 mcg/dL) at Cmax (60 minutes post-dose).

Effect of Food
The coadministration of ALKINDI SPRINKLE with soft food (yogurt and fruit puree) has been studied in healthy adult male volunteers, where it was shown to be bioequivalent to administration of dry granules directly to the back of the tongue.

Distribution
90% or more of circulating hydrocortisone is reversibly bound to protein.

The binding is accounted for by two protein fractions. One, corticosteroid-binding globulin is a glycoprotein; the other is albumin.

Elimination
Hydrocortisone is metabolized in the liver and most body tissues to hydrogenated and degraded forms such as tetrahydrocortisone and tetrahydrocortisol which are excreted in the urine, mainly conjugated as glucuronides, together with a very small proportion of unchanged hydrocortisone.

The terminal half-life of hydrocortisone is about 1.5 hours following intravenous and oral dosing of hydrocortisone tablets and ALKINDI SPRINKLE in dexamethasone-suppressed healthy adult male volunteers.

13 NONCLINICAL TOXICOLOGY

13.1 Carcinogenesis, Mutagenesis, Impairment of Fertility

No adequate studies in animals have been conducted with hydrocortisone to evaluate carcinogenic or mutagenic potential. Corticosteroids have been shown to impair fertility in male rats.

16 HOW SUPPLIED/STORAGE AND HANDLING

ALKINDI SPRINKLE oral granules are supplied as white to off-white granules in transparent capsules as follows:

Strength | Imprint on Capsules | Amount in Bottle | NDC
0.5 mg | “INF-0.5” in red ink | 50 capsules | 71863-109-50
1 mg | “INF-1.0” in blue ink | 50 capsules | 71863-110-50
2 mg | “INF-2.0” in green ink | 50 capsules | 71863-111-50
5 mg | “INF-5.0” in gray ink | 50 capsules | 71863-112-50

Store at controlled room temperature (USP) 20°C to 25°C (68°F to 77°F). Excursions permitted to 15°C to 30 °C (59°F to 86°F). Store in the original bottle in order to protect from light.

Once the bottle has been opened, use the capsules within 60 days.

17 PATIENT COUNSELING INFORMATION

Advise the caregiver or patient to read the FDA-approved patient labeling (Medication Guide).

Adrenal Crisis

Inform the patient or caregiver that undertreatment or sudden discontinuation of ALKINDI SPRINKLE may lead to symptoms of adrenocortical insufficiency, adrenal crisis, and death. Advise the caregiver that the potential dosing inaccuracy of manipulated oral hydrocortisone preparations (e.g., split or crushed tablets or compounded suspension) may result in differences. When switching treatment from conventional oral hydrocortisone to ALKINDI SPRINKLE, advise the patient or caregiver that this could lead to unintended clinical consequences and recommend close monitoring of patients after the switch. Inform the patient or caregiver to contact their healthcare provider if they have prolonged vomiting, are severely ill or are unable to take oral medications. [see Warnings and Precautions (5.1)]

Immunosuppression and Increased Risk of Infections

Advise patients and/or caregivers that greater than replacement dosage of corticosteroids can

suppress the immune system and increase the risk of infections. Instruct patients and/or

caregivers to contact their healthcare provider if they develop any infections [see Warnings and

Precautions (5.2)]

Administration Information

Advise the patient or caregiver that ALKINDI SPRINKLE is a granule formulation contained in a capsule. Do not swallow the capsule. Do not chew or crush the granules. Open the capsule and give the granules directly into the patient’s mouth. Alternatively, sprinkle the granules onto soft food and give immediately as the taste masking cover can dissolve in as little as 5 minutes. Avoid wetting the capsule as this may cause some granules to stick to the capsule. Immediately following administration, take a sip of fluids to ensure all granules have been swallowed. [see Dosage and Administration (2.3)].

Growth Retardation

Discuss with the caregiver that long-term use of corticosteroids in excessive doses may cause growth retardation in pediatric patients. [see Warnings and Precautions (5.3)]

Cushing’s Syndrome

Inform patients and caregivers that prolonged use of corticosteroids in supraphysiologic doses may cause Cushing’s syndrome and that symptoms and signs include weight gain, decreased height velocity, hyperglycemia, hypertension, edema, easy bruising, muscle weakness, red round face, depression or mood swings. [see Warnings and Precautions (5.4)]

Decrease in Bone Mineral Density

Inform the patient or caregiver that corticosteroids decrease bone formation and increase bone resorption that may lead to osteoporosis. [see Warnings and Precautions (5.5)]

Psychiatric Adverse Reactions

Advise the patient or caregiver that corticosteroid use may be associated with severe psychiatric adverse reactions such as euphoria, mania, psychosis with hallucinations or depression. Instruct caregivers and/or patients to seek medical advice if psychiatric symptoms develop. [see Warnings and Precautions (5.6)]

Ophthalmic Adverse Reactions

Inform patients or caregivers that ophthalmic effects such as cataract, glaucoma or central serous chorioretinopathy have been reported with prolonged use of high-dose corticosteroids. Instruct patients or caregivers to report any blurred vision or visual disturbances to their healthcare provider. [see Warnings and Precautions (5.7)]

Gastrointestinal Adverse Reactions

Discuss with patients or caregivers that use of corticosteroids may increase risk of gastrointestinal perforation in certain gastrointestinal disorders [see Warnings and Precautions (5.8)].

Excretion of Granules

ALKINDI SPRINKLE granules may sometimes be seen in stools since the center of the granule is not absorbed in the gut after the active substance has been released. Inform patients or caregivers that this does not mean the product is ineffective and they should not take another dose.

ALKINDI SPRINKLE is manufactured for Eton Pharmaceuticals, Inc. by Glatt Pharmaceutical Services GmbH & Co. KG Werner-Glatt-Strasse 1, Binzen, Baden-Wuerttemberg, 79589, Germany.

ALKINDI SPRINKLE®is a registered trademark of Neurocrine UK Limited.

ALKINDI is covered by the following US patents: 9,649,280; 9,675,559; 9,717,740; and other patents in other countries internationally.

ALKINDI SPRINKLE is distributed in the USA by Eton Pharmaceuticals, Inc. under license from Neurocrine UK Limited.

Medication Guide

ALKINDI SPRINKLE® (ælˈkɪndi spr-en-kle)

(hydrocortisone) oral granules

Read this Medication Guide before you start giving ALKINDI SPRINKLE to your child, and each time your child gets a

refill. There may be new information. This information does not take the place of talking to your healthcare provider about your child’s medical condition or treatment.

What is the most important information I should know about ALKINDI SPRINKLE?

ALKINDI SPRINKLE may cause serious side effects, including:

Adrenal gland problems.Not giving enough ALKINDI SPRINKLE, stopping ALKINDI SPRINKLE, or switching to ALKINDI SPRINKLE after taking another hydrocortisone medicine (the same class of medicines as ALKINDI SPRINKLE) by mouth, can cause serious and life-threatening adrenal gland problems including death. Do not stop giving ALKINDI SPRINKLE without talking to your healthcare provider. Tell your healthcare provider if your child has any of these symptoms:

1. loss of appetite
2. joint pain
3. low blood sugar
4. fatigue
5. nausea
6. feeling lightheaded or dizzy
7. weakness
8. vomiting
9. problems with body salt (electrolyte) levels

Your healthcare provider will change the dose of ALKINDI SPRINKLE depending on your child’s size. Tell your healthcare provider if your child cannot swallow medicines by mouth. During episodes of acute infections, surgery, major trauma or if your child cannot take medicines by mouth, your healthcare provider may recommend increased doses of ALKINDI SPRINKLE or use of corticosteroid medicines given directly into the bloodstream instead.

The amount of hydrocortisone in a dose of ALKINDI SPRINKLE may not be the same as in previous hydrocortisone medicines that your child takes by mouth if these oral hydrocortisone medicines have been changed (for example, crushed or compounded). When switching to ALKINDI SPRINKLE, your healthcare provider may need to prescribe a starting dose of ALKINDI SPRINKLE that is different from previous hydrocortisone medicines that your child may have been taking by mouth. Watch your child closely after being switched to ALKINDI SPRINKLE and contact your healthcare provider if your child has any symptoms of adrenal gland problems. Your healthcare provider may need to change the dose of ALKINDI SPRINKLE.

See “What are the possible side effects of ALKINDI SPRINKLE?” for more information about side effects.

What is ALKINDI SPRINKLE?

ALKINDI SPRINKLE is a prescription medicine that contains a medicine hydrocortisone. Hydrocortisone belongs to a group of medicines known as corticosteroids. Hydrocortisone is a synthetic version of the hormone cortisol. Cortisol is made naturally by the adrenal glands in the body. ALKINDI SPRINKLE (hydrocortisone) is a man-made (synthetic) corticosteroid used to replace the body’s cortisol when the adrenal glands do not make enough (adrenal insufficiency) in

children from birth to 17 years of age.

Who should not take or be given ALKINDI SPRINKLE?

Do not give your child ALKINDI SPRINKLE if they:

- are allergic to hydrocortisone or any of the ingredients in ALKINDI SPRINKLE. See the end of this Medication Guide for a complete list of ingredients in ALKINDI SPRINKLE.
- have any reaction like swelling or shortness of breath after being given ALKINDI SPRINKLE. Get medical help right away and tell your healthcare provider as soon as possible as these can be signs of an allergic reaction.

What should I tell my healthcare provider before giving ALKINDI SPRINKLE?

Before you give your child ALKINDI SPRINKLE, tell your healthcare provider about all of your child’s medical conditions, including if they:

- are feeling unwell, or their body is under stress because of surgery or trauma. Your healthcare provider may need to increase the dose of ALKINDI SPRINKLE for a short period of time.
- have a fever or infection.
- have nausea, vomiting, or diarrhea.
- are due for vaccinations. Taking ALKINDI SPRINKLE should not stop your child from being vaccinated. Tell your healthcare provider when your child is due for vaccinations.
- are scheduled for surgery.
- cannot swallow medicines by mouth or are fed through a nasogastric or gastric tube.
- are pregnant or plan to become pregnant. It is not known if ALKINDI SPRINKLE will harm your child’s unborn baby. Talk to your child’s healthcare provider if your child is pregnant or plans to become pregnant.
- are breastfeeding or plan to breastfeed. It is not known if ALKINDI SPRINKLE passes into the breast milk. You and your child’s healthcare provider should decide if your child will receive ALKINDI SPRINKLE while your child breastfeeds.

Tell your healthcare provider about all the medicines your child takes, including prescription and over-the-counter medicines, vitamins, and herbal supplements.

Some medicines, food and drink can affect the way that ALKINDI SPRINKLE works and may mean that your healthcare

provider needs to change your child’s dose of ALKINDI SPRINKLE.

Especially tell your healthcare provider if your child:

- takes medicines used to treat fungal infections such as itraconazole, posaconazole, and voriconazole.
- takes medicines used to treat bacterial infections such as rifampicin, rifabutin, erythromycin, andclarithromycin.
- takes medicines used to treat human immunodeficiency virus (HIV) infection and AIDS such as ritonavir, efavirenz, and nevirapine.
- takes seizure medicines such as phenytoin, carbamazepine, oxcarbazepine, phenobarbital, and primidone.
- takes estrogen.
- takes warfarin.
- takes nonsteroidal anti-inflammatory medicines such as aspirin, ibuprofen.
- takes cyclosporine.
- takes diabetes medicines.
- drinks grapefruit juice.

Know the medicines your child takes. Keep a list of them to show your healthcare provider and pharmacist when your child gets a new medicine.

How should I give ALKINDI SPRINKLE?

- See the detailed Instructions for Use that comes with your ALKINDI SPRINKLE for information on how to give a dose of ALKINDI SPRINKLE the right way.
- Give ALKINDI SPRINKLE exactly as prescribed by your healthcare provider.
- Do notstop giving ALKINDI SPRINKLE without talking to your healthcare provider. See “ What is the most important information I should know about ALKINDI SPRINKLE?”
- Do notlet your child chew or crush the granules. Do not let your child swallow the capsule.
- Do notlet the capsules get wet as this may make some of the granules stick to the capsule.
- Call your healthcare provider if granules come back up into your child’s mouth (regurgitation) or your child has vomiting after swallowing ALKINDI SPRINKLE. Your child may not have received the full dose of ALKINDI SPRINKLE and another dose of ALKINDI SPRINKLE may be needed.
- Your child may sometimes pass the ALKINDI SPRINKLE granules in their stools (bowel movement). It does not mean that ALKINDI SPRINKLE is not working. Do notgive your child another dose of ALKINDI SPRINKLE.
- ALKINDI SPRINKLE granules should not be given through a nasogastric tube because the granules may block the tube.
- If your child takes too much ALKINDI SPRINKLE, call your healthcare provider right away or go to the nearest emergency room.

What are the possible side effects of ALKINDI SPRINKLE?

ALKINDI SPRINKLE may cause serious side effects, including:

- See “What is the most important information I should know about ALKINDI SPRINKLE?”
- Weakened immune system and increased risk of Infections.Taking too much ALKINDI SPRINKLE can weaken your body's immune system and increase your change of getting infections. Tell your healthcare provider if your child has any infection or has any of these symptoms:

1. fever
2. stomach area (abdominal) pain
3. cough
4. diarrhea
5. flu-like symptoms

- Slowed growth in children.Taking too much ALKINDI SPRINKLE and taking it for long periods of time can affect your child’s growth. Tell your healthcare provider if you are worried about your child’s growth. Your healthcare provider will change the dose depending on your child’s size.
- Cushing’s syndrome.Taking too much ALKINDI SPRINKLE and taking it for long periods of time can cause Cushing’s syndrome. Tell your healthcare provider if your child has any of these symptoms:

1. weight gain
2. high blood sugar
3. swelling
4. muscle weakness
5. feeling depressed
6. slowed growth in height
7. high blood pressure
8. bruising easily
9. red, round face
10. mood swings

- Weak, brittle, or soft bones.ALKINDI SPRINKLE can affect your child’s bones. Your healthcare provider will change the dose depending on your child’s size and will monitor your child’s growth and bones.
- Changes in behavior.Your child’s behavior may change after starting or during treatment with ALKINDI

SPRINKLE. Tell your healthcare provider right away if your child develops any changes inbehavior including:

strong feelings of happiness and excitement
overexcited and overactivity
loss of contact with reality, with feelings that are not real, and mental confusion
depression

- Vision problems.Tell your healthcare provider if your child develops blurred vision or other vision problems during treatment with ALKINDI SPRINKLE. Your healthcare provider may have your child see an eye doctor.
- Gastrointestinal problems.ALKINDI SPRINKLE can affect your child’s stomach or intestine. Tell your healthcare provider if your child has gastrointestinal illnesses such as stomach or intestinal ulcers, infections, or gastrointestinal surgery.
- Vaccinations.Administration of live vaccine may be acceptable while taking ALKINDI SPRINKLE.

The most common side effects of ALKINDI SPRINKLE include:

1. fluid retention
2. change in blood sugar (glucose) tolerance
3. increase in blood pressure
4. behavioral and mood changes
5. increased appetite and weight gain

These are not all the possible side effects of ALKINDI SPRINKLE. Call your doctor for medical advice about side effects. You may report side effects to FDA at 1-800-FDA-1088.

How should I store ALKINDI SPRINKLE?

- Store ALKINDI SPRINKLE at room temperature between 68°F to 77°F (20°C to 25°C).
- Store in the original bottle to protect from light.
- After the bottle has been opened, use the ALKINDI SPRINKLE capsules within 60 days.

Keep ALKINDI SPRINKLE and all medicines out of the reach of children.

General information about the safe and effective use of ALKINDI SPRINKLE.

Medicines are sometimes prescribed for purposes other than those listed in a Medication Guide. Do not use ALKINDI SPRINKLE for a condition for which it was not prescribed. Do not give ALKINDI SPRINKLE to other people, even if they

have the same symptoms that you have. It may harm them. You can ask your pharmacist or healthcare provider for information about ALKINDI SPRINKLE that is written for health professionals.

What are the ingredients in ALKINDI SPRINKLE?

Active ingredient:hydrocortisone

Inactive ingredients:

granules: microcrystalline cellulose, hypromellose, magnesium stearate, ethyl cellulose.

capsule: hypromellose

printing ink: shellac, propylene glycol, concentrated ammonia solution.

ALKINDI SPRINKLE is manufactured for Eton Pharmaceuticals, Inc. by Glatt Pharmaceutical Services GmbH & Co. KG Werner-Glatt-Strasse 1, Binzen, Baden- Wuerttemberg, 79589, Germany

ALKINDI SPRINKLE® is a registered trademark of Neurocrine UK Limited.

ALKINDI is covered by the following US patents: 9,649,280; 9,675,559; 9,717,740; and other patents in other countries internationally. For more information, go to www.alkindisprinkle.com or call 1-833-343-2500.

This Medication Guide has been approved by the U.S. Food and Drug Administration

Revised 12/2024

Instructions for Use

ALKINDI SPRINKLE®(ælˈkɪndi spr-en-kle)
(hydrocortisone) oral granules

Read this Instructions for Use before you start using ALKINDI SPRINKLE, and each time you get a refill. There may be new information. This information does not take the place of talking to your healthcare provider about your child’s medical condition or treatment.

Important information you need to know before giving ALKINDI SPRINKLE

- ALKINDI SPRINKLE comes in a capsule that must be opened before use.
- Do notlet your child swallow the capsule. Small children may choke.
- Do notlet your child chew or crush the granules in the capsule.
- Do notlet the capsules get wet as this may make some of the granules stick to the capsule.
- Your healthcare provider will decide the right dose of ALKINDI SPRINKLE for your child. Follow your healthcare provider’s instructions for the dose of ALKINDI SPRINKLE to give your child.
- Ask your healthcare provider or pharmacist if you are not sure how to prepare or give the prescribed dose of ALKINDI SPRINKLE to your child.
- Call your healthcare provider if granules come back up into your child’s mouth (regurgitation) or your child has vomiting after swallowing ALKINDI SPRINKLE. Your child may not have received the full dose of ALKINDI SPRINKLE and another dose of ALKINDI SPRINKLE may be needed.
- Your child may sometimes pass the ALKINDI SPRINKLE granules in their stools (bowel movement). It does not mean that ALKINDI SPRINKLE is not working. Do not give your child another dose of ALKINDI SPRINKLE.

Supplies needed to give ALKINDI SPRINKLE:

- ALKINDI SPRINKLE capsule(s) for prescribed dose
- 1 spoon
- soft food such as yogurt or pureed fruit or sip of fluids such as water, milk, breastmilk or formula

Preparing and giving ALKINDI SPRINKLE:

Step 1:Check the expiration date on the ALKINDI SPRINKLE bottle. Do not use ALKINDI SPRINKLE after the expiration date on the bottle has passed.

Step 2:Remove the prescribed dose of ALKINDI SPRINKLE capsules from the bottle.

Step 3:Hold and Tap
Hold the capsule with the writing at the top. Tap the capsule to make sure the granules fall to the bottom.

Step 4:Squeeze
Gently squeeze the bottom of the capsule to loosen the top of the capsule from the bottom.

Step 5:Twist
Carefully twist off the top of the capsule.

Step 6: Giving ALKINDI SPRINKLE

ALKINDI SPRINKLE can be given (a) with food onto a spoon, (b) without food onto a spoon, or (c) directly into the child’s mouth.

Do notadd the granules to a fluid before giving ALKINDI SPRINKLE because it can result in less than the full dose given and it may leave a bitter taste in the mouth.

(a) With food onto a spoon
Pour allgranules from each capsule directly onto a spoonful of cold or room temperature soft food (such as yogurt or fruit puree) and give right away.

(b) Without food onto a spoon
Pour allgranules directly onto a spoon and place them in the child’s mouth.

(c) Directly onto the child’s tongue.

Pour allgranules that make up the prescribed dose directly onto the child’s tongue.

Tap the capsule to make sure all granules are removed.

The ALKINDI SPRINKLE granules should be given and swallowed within 5 minutes to avoid a bitter taste.

Step 7: Give Fluids

After giving ALKINDI SPRINKLE, give a sip of fluids such as water, milk, breastmilk or formula right away to make sure all granules are swallowed.

Throwing Away (disposal of) ALKINDI SPRINKLE:

Ask your pharmacist how to throw away medicines you no longer use.

How should I store ALKINDI SPRINKLE?

- Store ALKINDI SPRINKLE at room temperature between 68°F to 77°F (20°C to 25°C).
- Store in the original bottle to protect from light.
- After the bottle has been opened, use the ALKINDI SPRINKLE capsules within 60 days.

Keep ALKINDI SPRINKLE and all medicines out of the reach of children.

ALKINDI SPRINKLE is manufactured for Eton Pharmaceuticals, Inc. by Glatt Pharmaceutical Services GmbH & Co. KG Werner-Glatt-Strasse 1, Binzen, Baden-Wuerttemberg, 79589, Germany

ALKINDI SPRINKLE® is a registered trademark of Neurocrine UK Limited.

ALKINDI is covered by the following US patents: 9,649,280; 9,675,559; 9,717,740; and other patents in other countries internationally.

For more information, go to www.alkindisprinkle.comor call 1-833-343-2500.

This Instructions for Use has been approved by the U.S. Food and Drug Administration.

Revised: 12/2024

PRINCIPAL DISPLAY PANEL

Alkindi Sprinkle (hydrocortisone) oral granules 0.5 mg - NDC 71863-109-50 - 50 Tablets Carton Label

Alkindi Sprinkle (hydrocortisone) oral granules 0.5 mg - NDC 71863-109-50 - 50 Tablets Container Label

Alkindi Sprinkle (hydrocortisone) oral granules 1 mg - NDC 71863-110-50 - 50 Tablets Carton Label

Alkindi Sprinkle (hydrocortisone) oral granules 1 mg - NDC 71863-110-50 - 50 Tablets Container Label

Alkindi Sprinkle (hydrocortisone) oral granules 2 mg - NDC 71863-111-50 - 50 Tablets Carton Label

Alkindi Sprinkle (hydrocortisone) oral granules 2 mg - NDC 71863-111-50 - 50 Tablets Container Label

Alkindi Sprinkle (hydrocortisone) oral granules 5 mg - NDC 71863-112-50 - 50 Tablets Carton Label

Alkindi Sprinkle (hydrocortisone) oral granules 5 mg - NDC 71863-112-50 - 50 Tablets Container Label

Alkindi Sprinkle (hydrocortisone) oral granules 0.5 mg Samples - NDC 71863-117-50 - 50 Tablets Container Label

Alkindi Sprinkle (hydrocortisone) oral granules 1 mg Samples - NDC 71863-118-50 - 50 Tablets Container Label